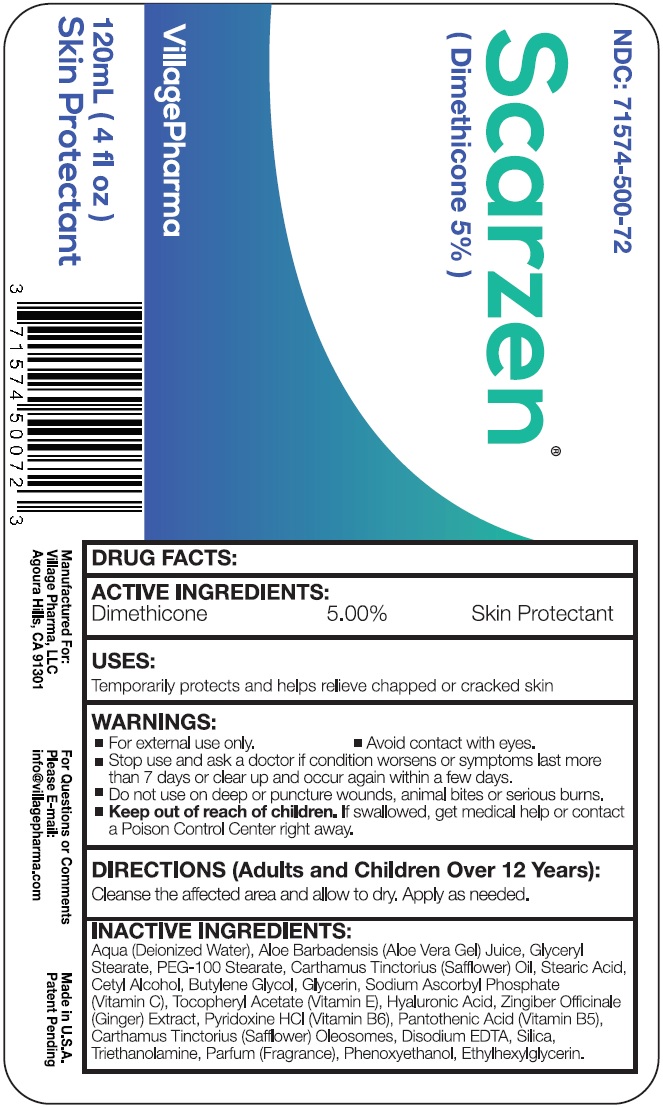 DRUG LABEL: Scarzen
NDC: 71574-500 | Form: LOTION
Manufacturer: Village Pharma LLC
Category: otc | Type: HUMAN OTC DRUG LABEL
Date: 20260101

ACTIVE INGREDIENTS: DIMETHICONE, UNSPECIFIED 50 mg/1 mL
INACTIVE INGREDIENTS: WATER; ALOE VERA LEAF; GLYCERYL MONOSTEARATE; PEG-100 MONOSTEARATE; STEARIC ACID; CETYL ALCOHOL; BUTYLENE GLYCOL; GLYCERIN; SODIUM ASCORBYL PHOSPHATE; HYALURONIC ACID; GINGER; PYRIDOXINE HYDROCHLORIDE; PANTOTHENIC ACID; SAFFLOWER; EDETATE DISODIUM ANHYDROUS; SILICON DIOXIDE; TROLAMINE; PHENOXYETHANOL; ETHYLHEXYLGLYCERIN

Scarzen (Dimethicone 5%)

ACTIVE INGREDIENTS:

Dimethicone 5.00%

PURPOSE

Skin Protectant

USES:

Temporarily protects and helps relieve chapped or cracked skin

WARNINGS:

- For external use only.
- Avoid contact with eyes.

Stop use and ask a doctor

- if condition worsens or symptoms last more than 7 days or clear up and occur again within a few days.

Do not use

on deep or puncture wounds, animal bites or serious burns.

Keep out of reach of children.

If swallowed, get medical help or contact a Poison Control Center right away.

DIRECTIONS (Adults and Children Over 12 Years):

Cleanse the affected area and allow to dry. Apply as needed.

INACTIVE INGREDIENTS:

Aqua (Deionized Water), Aloe Barbadensis (Aloe Vera Gel) Juice, Glyceryl Stearate, PEG-100 Stearate, Carthamus Tinctorius (Sunflower) Oil, Stearic Acid, Cetyl Alcohol, Butylene Glycol, Glycerin, Sodium Ascorbyl Phosphate (Vitamin C), Tocopheryl Acetate (Vitamin E), Hyaluronic Acid, Zingiber Officinale (Ginger) Extract, Pyridoxine HCL (Vitamin B6), Pantothenic Acid (Vitamin B5), Carthamus Tinctorius (Safflower) Oleosomes, Disodium EDTA, Silica, Triethanolamine, Parfum (Fragrance), Phenoxyethanol, Ethylhexylglycerin.